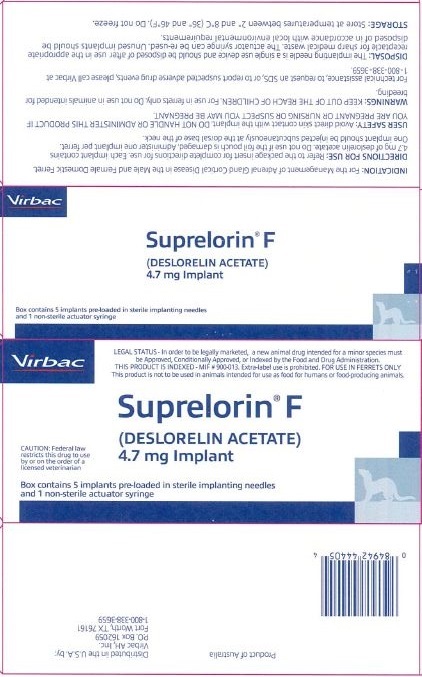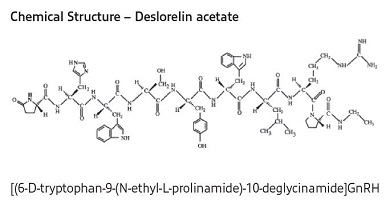 DRUG LABEL: Suprelorin F
NDC: 51311-444 | Form: IMPLANT
Manufacturer: Virbac AH, Inc.
Category: animal | Type: PRESCRIPTION ANIMAL DRUG LABEL
Date: 20220107

ACTIVE INGREDIENTS: deslorelin acetate 4.7 mg/1 1

Suprelorin® F
(DESLORELIN ACETATE) 4.7 mg Implant

LEGAL STATUS - In order to be legally marketed, a new animal drug intended for a minor species must be Approved, Conditionally
Approved, or Indexed by the Food and Drug Administration. THIS PRODUCT IS INDEXED - MIF # 900-013. Extra-label use is prohibited. FOR USE IN FERRETS ONLY This product is not to be used in animals intended for use as food for humans or food-producing animals.

CAUTION

Federal (USA) law restricts this drug to use by or on the order of a licensed veterinarian.

DESCRIPTION

Suprelorin® F (4.7 mg) Implant is a synthetic GnRH analogue (deslorelin acetate) in a biocompatible, slow release subcutaneous implant. The implant is a solid, opaque, white to pale yellow cylinder, 2.3 mm x 12.5 mm in length and weighing 50 mg. The Suprelorin® F (4.7 mg) Implant comes pre-loaded in an implanting needle. Each implant contains 4.7 mg deslorelin (as deslorelin acetate) in an inert matrix.

INDICATIONS

Suprelorin® F (4.7 mg) Implant is indicated for the management of adrenal gland cortical disease in the male and female domestic ferret.

DOSAGE AND ADMINISTRATION

The recommended dosage is one, 4.7 mg implant per ferret every 12 months. Appropriate clinical monitoring is suggested to determine that the symptoms of adrenal disease are being adequately controlled.

Do not use if the foil pouch is damaged.

Remove Luer Lock cap from the implanting needle. Attach the actuator syringe to the implanter using the luer lock connection. One implant should be implanting needle subcutaneously at the dorsal aspect of the base of the neck. Administer only one implant per ferret. Select the implant site by locating the area of the back midway between the shoulder blades. It is not necessary to prepare the implantation site. If the hair is long, a small section may be clipped if required. Lift the loose skin between the shoulder blades. Insert the entire length of the needle subcutaneously. Fully depress the actuator syringe plunger. Press the skin at the insertion site as the needle is slowly withdrawn, and maintain pressure for 30 seconds. Examine the implanting needle to verify that the implant has not remained within the needle, and that the blue plastic spacer is visible at the tip of the needle. It may be possible to palpate the implant in situ. The biocompatible implant does not require removal. Wash hands after use.

Repeat treatment every 12 months to maintain efficacy. Appropriate endocrine testing and clinical monitoring should be performed at appropriate intervals to monitor the response to therapy.

CONTRAINDICATIONS

Do not use this product in ferrets with known hypersensitivity to deslorelin acetate or other synthetic hormones.

HUMAN SAFETY WARNINGS

KEEP OUT OF REACH OF CHILDREN. DO NOT HANDLE THIS PRODUCT IF YOU ARE PREGNANT OR NURSING OR SUSPECT YOU MAY BE PREGNANT. Accidental administration may lead to a disruption of the menstrual cycle. Avoid direct skin contact with the implant; if skin contact occurs, wash the affected area immediately with soap and water. The use of gloves is advised. As with all injectable drugs causing profound physiological effects, routine precautions should be employed by practitioners when handling and using Suprelorin® F (4.7 mg) Implant to prevent accidental injection. In case of accidental human injection, a physician should be consulted and the implant should be removed.

PRECAUTION

Do not use in animals intended for breeding. The safe use of this product has not been evaluated in pregnant or lactating ferrets.

ADVERSE REACTIONS

It is possible that treated ferrets will exhibit signs of soreness and swelling at the implantation site which should resolve over one or two weeks. Undesirable histology at the site of implantation has not been reported in other species (canine). Other reported side effects include: weight gain, lethargy and failure to respond to therapy.

To report suspected adverse drug events, please call Virbac at 800-338-3659. For additional information about adverse drug experience reporting for animal drugs, contact the FDA at 1-888-FDA-VETS or www.fda.gov/reportanimalae.

PHARMACOLOGY

Suprelorin® F (4.7 mg) Implant is a controlled release implant containing the GnRH agonist deslorelin. Deslorelin acetate suppresses the reproductive endocrine system, preventing production of pituitary and gonadal hormones. Deslorelin acetate has not been shown to reduce the size of adrenal tumors and is not considered curative.

DISPOSAL

Each implanting needle (sterile) is a single use device. Used needles should immediately be placed in a designated and appropriately labeled "sharps" container. Each actuator syringe (non-sterile) is a multi-use device and should be saved for future use with the remaining implant(s) in the carton. Unused implants should be disposed of in accordance with local environmental requirements.

STORAGE

Store at temperatures between 2° and 8° C (36° and 46° F). Do not freeze.

HOW SUPPLIED

Five (5) or two (2) implants pre-loaded in implanting needles and individually packaged per carton.

For technical assistance, to request an SDS, or to report suspected adverse drug events, please call Virbac at 1-800-338-3659.

Manufactured for:
Virbac AH, Inc.
P.O. Box 162059
Fort Worth, TX 76161

Product of Australia

MIF 900-013

Revision 11/2020
L-2000-F-US-3